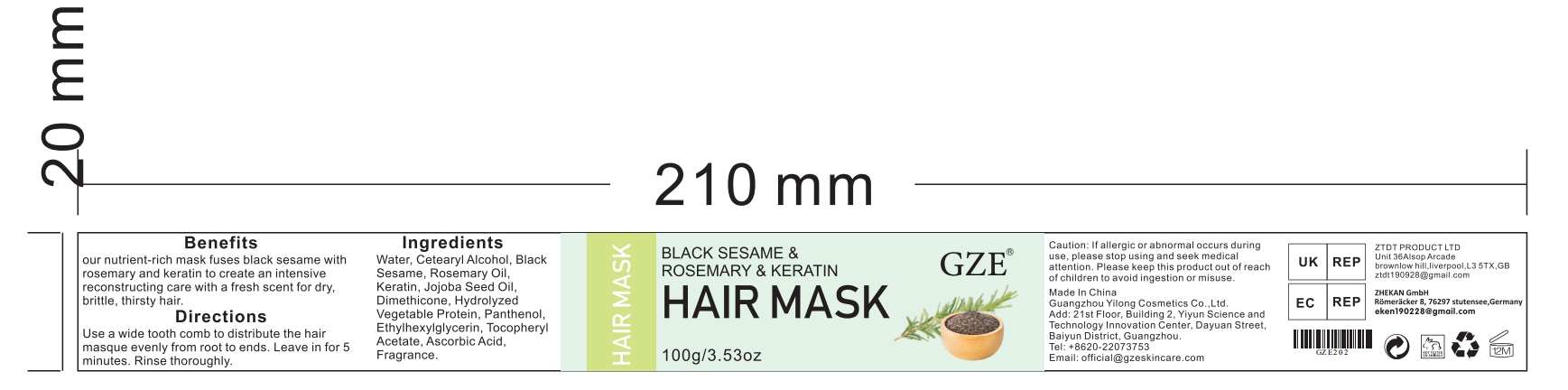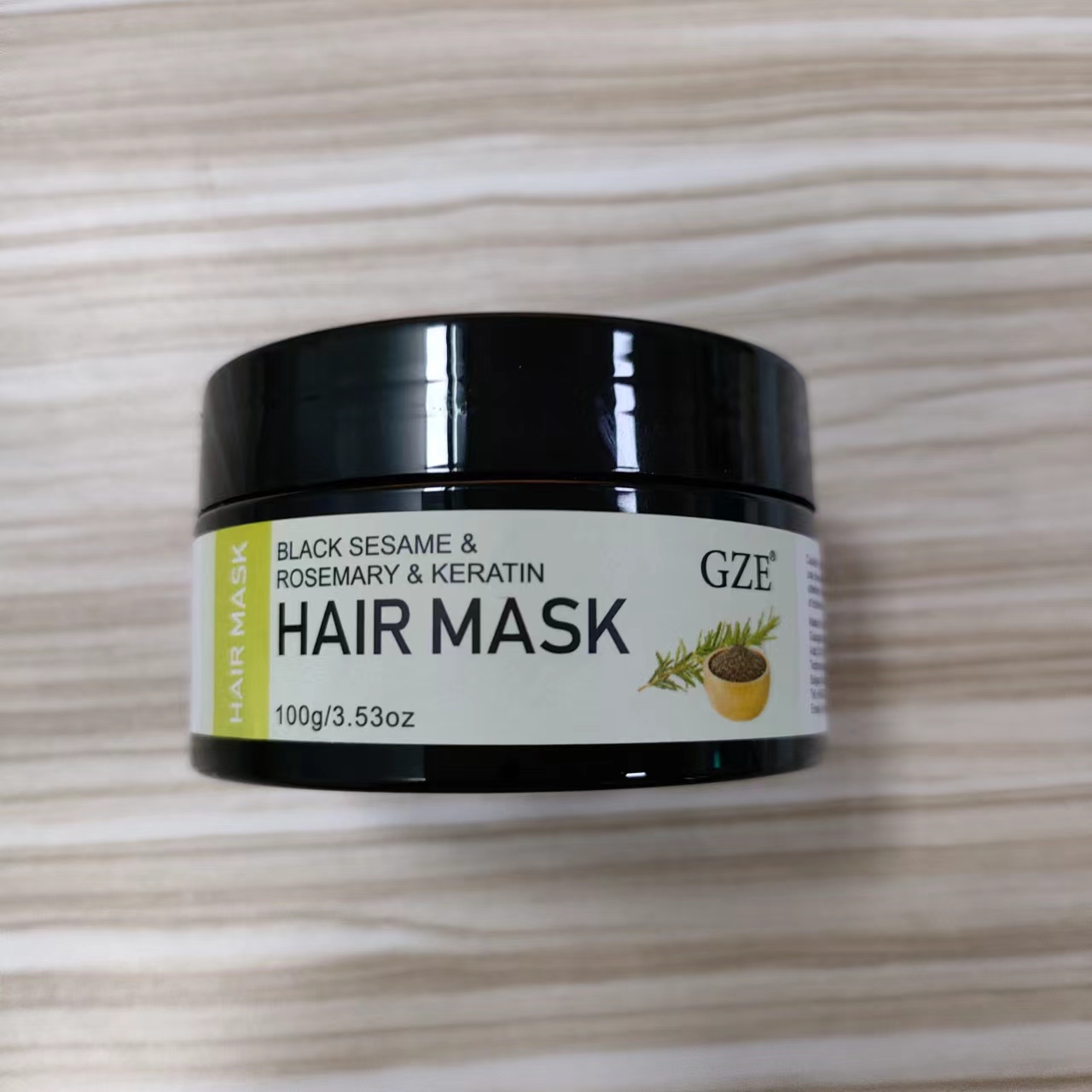 DRUG LABEL: GZE Black Sesame Rosemary Keratin Hair Mask
NDC: 83566-202 | Form: CREAM
Manufacturer: Guangzhou Yilong Cosmetics Co.,Ltd.
Category: otc | Type: HUMAN OTC DRUG LABEL
Date: 20240624

ACTIVE INGREDIENTS: ROSEMARY OIL 5 g/100 g; SIMMONDSIA CHINENSIS SEED 3 g/100 g; AMINO ACIDS, HAIR KERATIN 5 g/100 g; SESAME SEED 6 g/100 g
INACTIVE INGREDIENTS: ASCORBIC ACID; ETHYLHEXYLGLYCERIN; .ALPHA.-TOCOPHEROL ACETATE, D-; HYDROLYZED JOJOBA ESTERS (ACID FORM); DIMETHICONE; FRAGRANCE 13576; WATER; CETEARYL STEARATE; PANTHENOL

GZE Black Sesame Rosemary Keratin Hair Mask

ACTIVE INGREDIENT

ROSEMARY OIL
SESAME SEED
AMINO ACIDS, HAIR KERATIN
SIMMONDSIA CHINENSIS SEED

INACTIVE INGREDIENT

ASCORBIC ACID
ETHYLHEXYLGLYCERIN
.ALPHA.-TOCOPHEROL ACETATE, D-
HYDROLYZED JOJOBA ESTERS (ACID FORM)
DIMETHICONE
FRAGRANCE 13576
WATER
CETEARYL STEARATE
PANTHENOL

PURPOSE

Hair care

INDICATIONS AND USAGE

Use a wide tooth comb to distribute the hair masque evenly from root to ends. Leave in for 5 minutes. Rinse thoroughly.

WARNINGS

For external use only.

Stop use and ask a doctor if rash occurs.

Do not use on damaged or broken skin.

When using this product keep out of eyes. Rinse with water to remove.

Keep out of reach of children. If swallowed, get medical help or contact a Poison Control Center right away.

DOSAGE AND ADMINISTRATION

Use a wide tooth comb to distribute the hair masque evenly from root to ends. Leave in for 5 minutes. Rinse thoroughly.